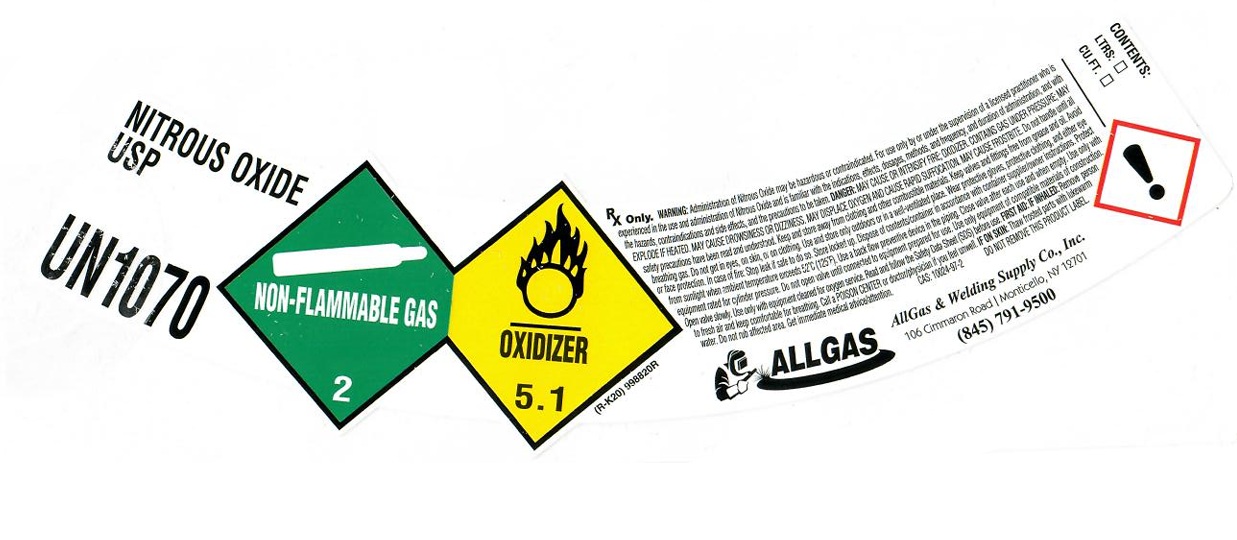 DRUG LABEL: Oxygen
NDC: 56130-004 | Form: GAS
Manufacturer: All Gas & Welding Supplies Co., Inc.
Category: prescription | Type: HUMAN PRESCRIPTION DRUG LABEL
Date: 20251216

ACTIVE INGREDIENTS: NITROUS OXIDE 992 mL/1 L

Nitrous Oxide

PACKAGE LABEL

NITROUS OXIDE USP

UN1070

Rx Only. WARNING: Administration of Nitrous Oxide may be hazardous or contraindicated. For use only by or under the supervision of a licensed practitioner who is experienced in the use and administration of Nitrous Oxide and is familiar with the indications, effects, dosages, methods, and frequency, and duration of administration, and with the hazards, contraindications and side effects, and the precautions to be taken. DANGER: MAY CAUSE OR INTENSIFY FIRE; OXIDIZER. CONTAINS GAS UNDER PRESSURE; MAY EXPLODE IF HEATED. MAY CAUSE DROWSINESS OR DIZZINESS. MAY DISPLACE OXYGEN AND CAUSE RAPID SUFFOCATION. MAY CAUSE FROSTBITE. Do not handle until all safety precautions have been read and understood. Keep and store away from clothing and other combustible materials. Keep valves and fittings free from grease and oil. Avoid breathing gas. Do not get in eyes, on skin, or on clothing. Use and store only outdoors or in a well-ventilated place. Wear protective gloves, protective clothing, and either eye or face protection. In case of fire: Stop leak if safe to do so. Store locked up. Dispose of contents/container in accordance with container supplier/owner instructions. Protect form sunlight when ambient temperature exceeds 52 C (125 F). Use a back flow preventive in the piping. Close valve after each use and when empty. Use only with equipment rated for cylinder pressure. Do not open valve until connected to equipment prepared for use. Use only equipment of compatible materials of construction. Open valve slowly. Use only with equipment cleaned for oxygen service. Read and follow the Safety Data Sheet (SDS) before use. FIRST AID: IF INHALED: Remove person to fresh air and keep comfortable for breathing. Call a POISON CENTER or doctor/physician if you feel unwell. IF ON SKIN: Thaw frosted parts with lukewarm water. Do not rub affected area. Get immediate medical advice/attention. CAS:10024-97-2 DO NOT REMOVE THIS PRODUCT LABEL.

ALLGAS

ALLGAS & Welding Supply Co., Inc.

106 Cimmaron Road Monticello, NY 12701

(845) 791-9500

CONTENTS: LTRS: CU.FT.